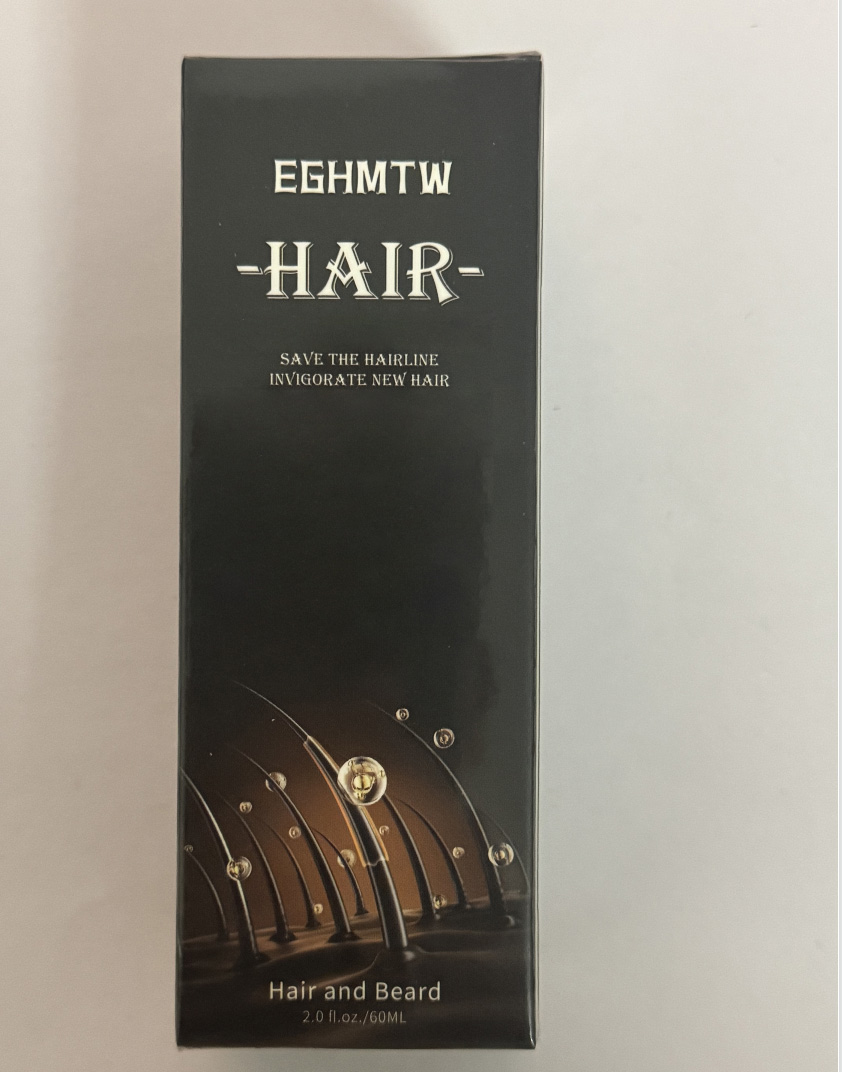 DRUG LABEL: EGHMTW hair oil
NDC: 84422-103 | Form: LIQUID
Manufacturer: Shenzhen Graceful Cosmetics Co., Ltd
Category: otc | Type: HUMAN OTC DRUG LABEL
Date: 20240805

ACTIVE INGREDIENTS: PROPYLENE GLYCOL 10 g/100 mL
INACTIVE INGREDIENTS: WATER; CENTELLA ASIATICA ROOT; SAURURUS CERNUUS WHOLE

DOSAGE AND ADMINISTRATION

Spray an appropriate amount on the roots of hair every day

WARNINGS

If you experience any discomfort, please stop using immediately

INACTIVE INGREDIENT

WATER, GLYCERIN, CENTELLA ASIATICA ROOTEXTRACT, SAURURUS CHINENSISLEAF/ROOT EXTRACT

INDICATIONS AND USAGE

Used for hair care

Stay away from places that children can reach

PURPOSE

Used for hair care